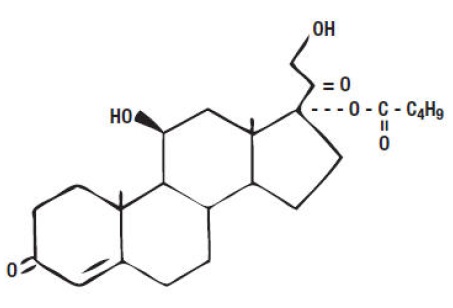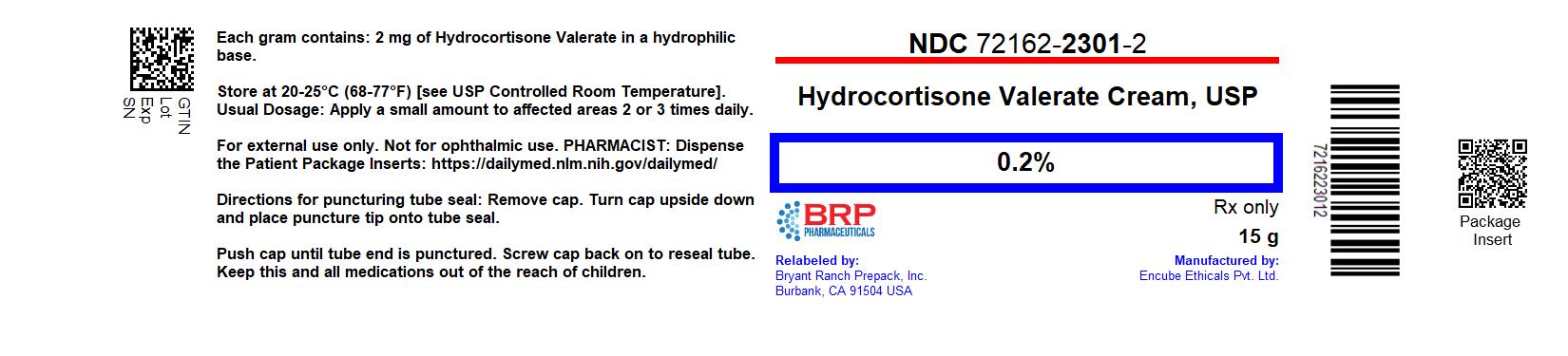 DRUG LABEL: hydrocortisone valerate cream
NDC: 72162-2301 | Form: CREAM
Manufacturer: Bryant Ranch Prepack
Category: prescription | Type: HUMAN PRESCRIPTION DRUG LABEL
Date: 20260122

ACTIVE INGREDIENTS: HYDROCORTISONE VALERATE 2 mg/1 g
INACTIVE INGREDIENTS: METHYLPARABEN; PROPYLENE GLYCOL; SODIUM PHOSPHATE, DIBASIC, UNSPECIFIED FORM; SODIUM LAURYL SULFATE; STEARYL ALCOHOL; WATER; WHITE PETROLATUM; CARBOMER HOMOPOLYMER TYPE C (ALLYL PENTAERYTHRITOL CROSSLINKED); STEARETH-100; POLYOXYL 20 CETOSTEARYL ETHER

Rx only
Hydrocortisone Valerate Cream USP, 0.2%
For Dermatologic Use Only. Not for Ophthalmic Use.

DESCRIPTION

Hydrocortisone valerate cream USP, 0.2% contain hydrocortisone valerate, 11,21-dihydroxy-17-[(1-oxopentyl)oxy]-(11β)-pregn-4-ene-3,20-dione, a synthetic corticosteroid for topical dermatologic use. The corticosteroids constitute a class of primarily synthetic steroids used topically as anti-inflammatory and antipruritic agents. Chemically, hydrocortisone valerate is C26H38O6. It has the following structural formula:

Hydrocortisone valerate has a molecular weight of 446.58. It is a white, crystalline solid, soluble in ethanol and methanol, sparingly soluble in propylene glycol and insoluble in water.
Each gram of hydrocortisone valerate cream USP, 0.2% contains 2 mg hydrocortisone valerate in a hydrophilic base composed of carbomer homopolymer type C, dibasic sodium phosphate, methylparaben, sodium lauryl sulfate, polyoxyethylene (100) stearyl ether, stearyl alcohol, white petrolatum, polyoxyl 2 stearyl ether, purified water and propylene glycol.

CLINICAL PHARMACOLOGY

Like other topical corticosteroids, hydrocortisone valerate has anti-inflammatory, antipruritic and vasoconstrictive properties. The mechanism of the anti-inflammatory activity of the topical steroids, in general, is unclear. However, corticosteroids are thought to act by the induction of phospholipase A2 inhibitory proteins, collectively called lipocortins. It is postulated that these proteins control the biosynthesis of potent mediators of inflammation such as prostaglandins and leukotrienes by inhibiting the release of their common precursor arachidonic acid. Arachidonic acid is released from membrane phospholipids by phospholipase A2.
Pharmacokinetics
The extent of percutaneous absorption of topical corticosteroids is determined by many factors including the vehicle and the integrity of the epidermal barrier. Occlusive dressings with hydrocortisone for up to 24 hours have not been demonstrated to increase penetration; however, occlusion of hydrocortisone for 96 hours markedly enhances penetration. Topical corticosteroids can be absorbed from normal intact skin. Inflammation and/or other disease processes in the skin may increase percutaneous absorption.
Studies performed with hydrocortisone valerate cream USP, 0.2% indicate that it is in the medium range of potency as compared with other topical corticosteroids.

INDICATIONS AND USAGE

Hydrocortisone valerate cream USP, 0.2% is medium potency corticosteroids indicated for the relief of the inflammatory and pruritic manifestations of corticosteroid responsive dermatoses in adult patients.

CONTRAINDICATIONS

Hydrocortisone valerate cream USP, 0.2% is contraindicated in those patients with a history of hypersensitivity to any of the components of the preparations.

PRECAUTIONS

General

Systemic absorption of topical corticosteroids can produce reversible hypothalamic-pituitary-adrenal (HPA) axis suppression with the potential for glucocorticosteroid insufficiency after withdrawal of treatment. Manifestations of Cushing's syndrome, hyperglycemia, and glucosuria can also be produced in some patients by systemic absorption of topical corticosteroids while on treatment.

Patients applying a topical steroid to a large surface area or to areas under occlusion should be evaluated periodically for evidence of HPA axis suppression. This may be done by using the ACTH stimulation, A.M. plasma cortisol, and urinary free cortisol tests.

Hydrocortisone valerate cream USP, 0.2% have produced mild, reversible adrenal suppression in adult patients when used under occlusion for 5 days, 15 grams twice a day over 25 to 60% body surface area or when used three times a day over 20 to 30% body surface area to treat psoriasis for 3-4 weeks.

If HPA axis suppression is noted, an attempt should be made to withdraw the drug, to reduce the frequency of application, or to substitute a less potent corticosteroid. Recovery of HPA axis function is generally prompt upon discontinuation of topical corticosteroids. Infrequently, signs and symptoms of glucocorticosteroid insufficiency may occur, requiring supplemental systemic corticosteroids. For information on systemic supplementation, see prescribing information for these products.

Pediatric patients may be more susceptible to systemic toxicity from equivalent doses due to their larger skin surface to body mass ratios. (See PRECAUTIONS -- Pediatric Use).

If irritation develops, hydrocortisone valerate cream USP, 0.2% should be discontinued and appropriate therapy instituted. Allergic contact dermatitis with corticosteroids is usually diagnosed by observing a failure to heal rather than noting a clinical exacerbation, as with most topical products not containing corticosteroids. Such an observation should be corroborated with appropriate diagnostic patch testing.

If concomitant skin infections are present or develop, an appropriate antifungal or antibacterial agent should be used. If a favorable response does not occur promptly, use of hydrocortisone valerate cream USP, 0.2% should be discontinued until the infection has been adequately controlled.

Information for Patients

Patients using topical corticosteroids should receive the following information and instructions:

1. This medication is to be used as directed by the physician. It is for external use only. Avoid contact with the eyes.
2. This medication should not be used for any disorder other than that for which it was prescribed.
3. The treated skin area should not be bandaged, otherwise covered or wrapped, so as to be occlusive unless directed by the physician.
4. Patients should report to their physician any signs of local adverse reactions.
5. Hydrocortisone valerate cream USP, 0.2% should not be applied in the diaper areas as diapers or plastic pants may constitute occlusive dressings. (See DOSAGE AND ADMINISTRATION).
6. This medication should not be used on the face, underarms, or groin areas unless directed by the physician.
7. As with other corticosteroids, therapy should be discontinued when control is achieved. If no improvement is seen within 2 weeks, contact the physician.

Laboratory Tests

The following tests may be helpful in evaluating patients for HPA axis suppression:

ACTH stimulation test

A.M plasma cortisol test

Urinary free cortisol test

Carcinogenesis, Mutagenesis, Impairment of Fertility

Long-term animal studies have not been performed to evaluate the carcinogenic potential of hydrocortisone valerate. Hydrocortisone valerate cream USP, 0.2% was shown to be non-mutagenic in the Ames-Salmonella/Microsome Plate Test. There are no studies which assess the effects of hydrocortisone valerate on fertility and general reproductiveperformance.

Pregnancy

Teratogenic Effects
Corticosteroids have been shown to be teratogenic in laboratory animals when administered systemically at relatively low dosage levels. Some corticosteroids have been shown to be teratogenic after dermal application in laboratory animals.

Dermal embryofetal developmental studies were conducted in rabbits and rats with hydrocortisone valerate cream, 0.2%. Hydrocortisone valerate cream, 0.2%, was administered topically for 4 hours/day, rather than the preferred 24 hours/day, during the period of organogenesis in rats (gestational days 5-16) and rabbits (gestational days 6-19). Topical doses of hydrocortisone valerate up to 9 mg/kg/day (54 mg/m2/day) were administered to rats and 5 mg/kg/day (60 mg/m^2/day) were administered to rabbits. In the absence of maternal toxicity, a significant increase in delayed skeletal ossification in foetuses was noted at 9 mg/kg/day [2.5× the Maximum Recommended Human Dose (MRHD) based on body surface area (BSA) comparisons] in the rat study. No malformations in the fetuses were noted at 9 mg/kg/day (2.5× MRHD based on BSA comparisons) in the rat study. Indicators of embryofetal toxicity, significant decrease in fetal weight at 2 mg/kg/day (1× MRHD based on BSA) and a significant increase in post-implantation loss and embryo resorption at 5 mg/kg (3× MRHD based on BSA), were noted in the rabbit study. A significant increase in delayed skeletal ossification in fetuses was noted at 5 mg/kg/day (3× the MRHD based on BSA comparisons) in the rabbit study. Increased numbers of fetal malformations (e.g., cleft palate, omphalocele and clubbed feet) were noted at 5 mg/kg/day (3× MRHD based on BSA comparisons) in the rabbit study.

There are no adequate and well-controlled studies in pregnant women. Hydrocortisone valerate cream USP, 0.2% should be used during pregnancy only if the potential benefit justifies the potential risk to the fetus.

Nursing Mothers

Systemically administered corticosteroids appear in human milk and could suppress growth, interfere with endogenous corticosteroid production, or cause other untoward effects. It is not known whether topical administration of corticosteroids could result in sufficient systemic absorption to produce detectable quantities in human milk. Because many drugs are excreted in human milk, caution should be exercised when hydrocortisone valerate cream USP, 0.2% is administered to a nursing woman.

Pediatric Use

Safety of this product in pediatric patients has not been established. There is no data on adrenal suppression and/or growth suppression.

Because of a higher ratio of skin surface area to body mass, pediatric patients are at a greater risk than adults of HPA axis suppression and Cushing's syndrome when they are treated with topical corticosteroids. They are therefore also at a greater risk of adrenal insufficiency during and/or after withdrawal of treatment. Adverse effects including striae have been reported with inappropriate use of topical corticosteroids in infants and children (See PRECAUTIONS).

HPA axis suppression, Cushing's syndrome, linear growth retardation, delayed weight gain, and intracranial hypertension have been reported in children receiving topical corticosteroids.Manifestations of adrenal suppression in children include low plasma cortisol levels, and an absence of response to ACTH stimulation. Manifestations of intracranial hypertension include bulging fontanelles, headaches, and bilateral papilledema.

Geriatric Use

Clinical studies of hydrocortisone valerate cream USP, 0.2% did not include sufficient numbers of subjects aged 65 and over to determine whether they respond differently from younger subjects. Other reported clinical experience has not identified differences in responses between the elderly and younger patients.

ADVERSE REACTIONS

Hydrocortisone Valerate Cream USP, 0.2%

The following local adverse reactions have been reported with topical corticosteroids, and they may occur more frequently with the use of occlusive dressings. These reactions are listed in an approximate decreasing order of occurrence: burning, itching, irritation, dryness, folliculitis, hypertrichosis, acneiform eruptions, hypopigmentation, perioral dermatitis, allergic contact dermatitis, maceration of the skin, secondary infection, skin atrophy, striae, and miliaria.

In controlled clinical studies involving pediatric patients one month to 2 years of age (n=29), the incidence of adverse experiences, regardless of relationship to the use of hydrocortisone valerate cream USP, 0.2%, was approximately 21%. Reported reactions included stinging (10%), eczema (7%), fungal infection (3%), and gastrointestinal disorder (3%).

In controlled clinical studies involving pediatric patients 2 to 12 years of age (n=153), the incidence of adverse experiences, regardless of relationship to the use of hydrocortisone valerate cream USP, 0.2%, was approximately 10%. Reported reactions included stinging (3%), burning skin (2%), infection (Body as a Whole) (2%). Skin irritation, eczema, pruritus, application site reaction, rash, rash maculopapular, and dry skin were all reported at incidences of approximately 1%.

To report SUSPECTED ADVERSE REACTIONS, contact Encube Ethicals Private Limited al 1-833-285-4151 or FDA at 1-800-FDA- 1088 or www.fda.gov/medwatch.

OVERDOSAGE

Topically applied hydrocortisone valerate cream USP, 0.2% can be absorbed in sufficient amounts to produce systemic effects (see PRECAUTIONS).

DOSAGE AND ADMINISTRATION

Hydrocortisone valerate cream USP, 0.2% should be applied to the affected area as a thin film two or three times daily depending on the severity of the condition.

As with other corticosteroids, therapy should be discontinued when control is achieved. If no improvement is seen within 2 weeks, reassessment of the diagnosis may be necessary.

Hydrocortisone valerate cream USP, 0.2% should not be used with occlusive dressings unless directed by a physician. Hydrocortisone valerate cream USP, 0.2% should not be applied in the diaper area if the patient requires diapers or plastic pants as these garments may constitute occlusive dressing.

HOW SUPPLIED

Hydrocortisone Valerate Cream USP, 0.2%, is supplied in:

- NDC 72162-2301-2: 15 g in a TUBE
- NDC 72162-2301-4: 45 g in a TUBE
- NDC 72162-2301-6: 60 g in a TUBE

STORAGE

Store at 20° – 25°C (68° – 77°F) [see USP Controlled Room Temperature].

Repackaged/Relabeled by:
Bryant Ranch Prepack, Inc.
Burbank, CA 91504

PACKAGE LABEL

Hydrocortisone Valerate 0.2% Cream